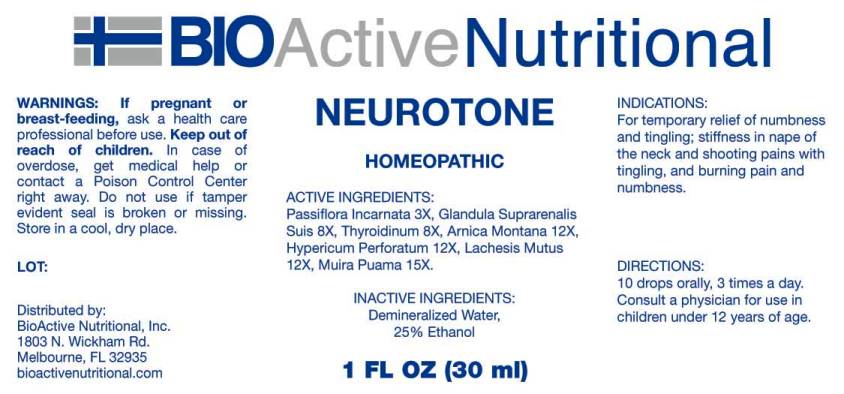 DRUG LABEL: Neurotone
NDC: 43857-0187 | Form: LIQUID
Manufacturer: BioActive Nutritional, Inc.
Category: homeopathic | Type: HUMAN OTC DRUG LABEL
Date: 20161207

ACTIVE INGREDIENTS: PASSIFLORA INCARNATA FLOWERING TOP 3 [hp_X]/1 mL; SUS SCROFA ADRENAL GLAND 8 [hp_X]/1 mL; SUS SCROFA THYROID 8 [hp_X]/1 mL; ARNICA MONTANA 12 [hp_X]/1 mL; HYPERICUM PERFORATUM 12 [hp_X]/1 mL; LACHESIS MUTA VENOM 12 [hp_X]/1 mL; PTYCHOPETALUM OLACOIDES ROOT 15 [hp_X]/1 mL
INACTIVE INGREDIENTS: WATER; ALCOHOL

Drug Facts:

ACTIVE INGREDIENTS:

Passiflora Incarnata 3X, Glandula Suprarenalis Suis 8X, Thyroidinum (Suis) 8X, Arnica Montana 12X, Hypericum Perforatum 12X, Lachesis Mutus 12X, Muira Puama 15X.

INDICATIONS:

For temporary relief of numbness and tingling; stiffness in nape of the neck and shooting pains with tingling, and burning pain and numbness.

WARNINGS:

If pregnant or breast-feeding, ask a health care professional before use.

Keep out of reach of children. In case of overdose, get medical help or contact a Poison Control Center right away.

Do not use if tamper evident seal is broken or missing.

Store in cool, dry place.

DIRECTIONS:

10 drops orally, 3 times a day. Consult a physician for use in children under 12 years of age.

INACTIVE INGREDIENTS:

Demineralized water, 25% Ethanol.

Keep out of reach of children. In case of overdose, get medical help or contact a Poison Control Center right away.

INDICATIONS:

For temporary relief of numbness and tingling; stiffness in nape of the neck and shooting pains with tingling, and burning pain and numbness.

QUESTIONS:

Distributed by:
BioActive Nutritional, Inc.
1803 N. Wickham Rd.
Melbourne, FL 32935
bioactivenutritional.com

PACKAGE LABEL DISPLAY:

BIOActive Nutritional

NEUROTONE

HOMEOPATHIC

1 FL OZ (30 ml)